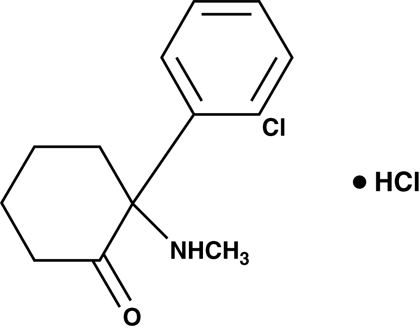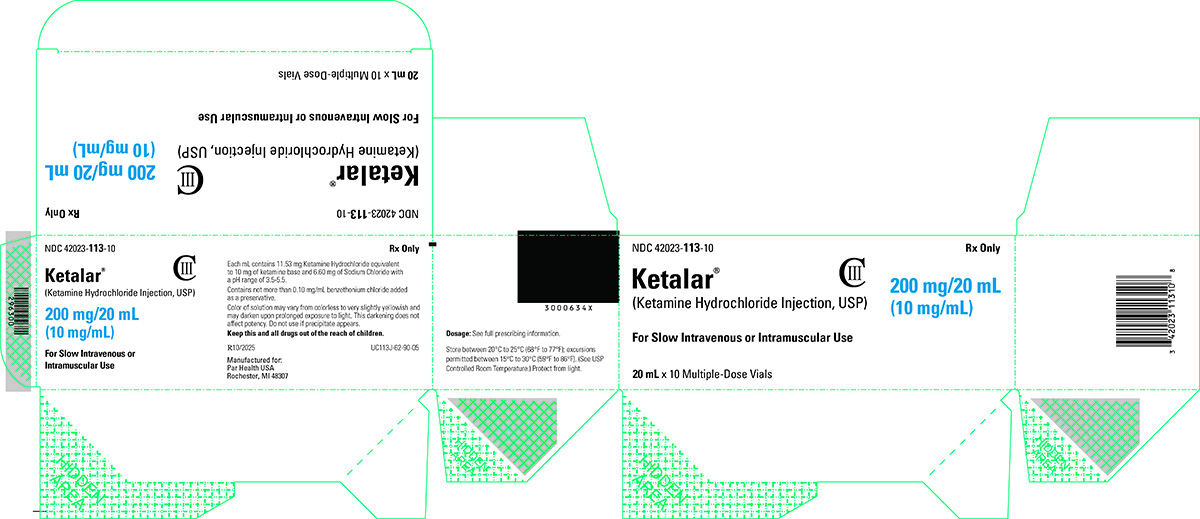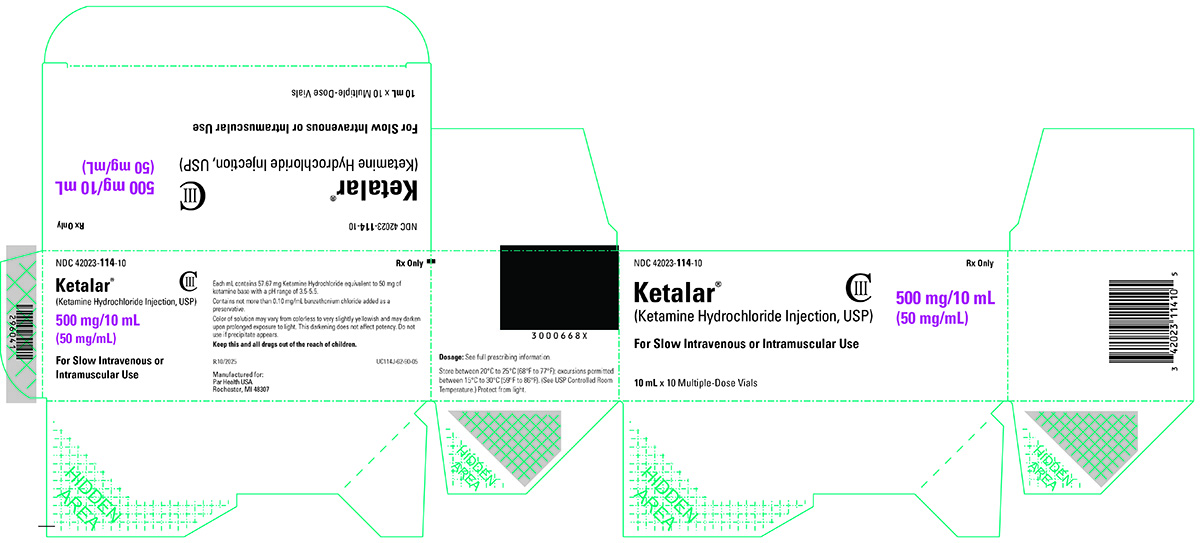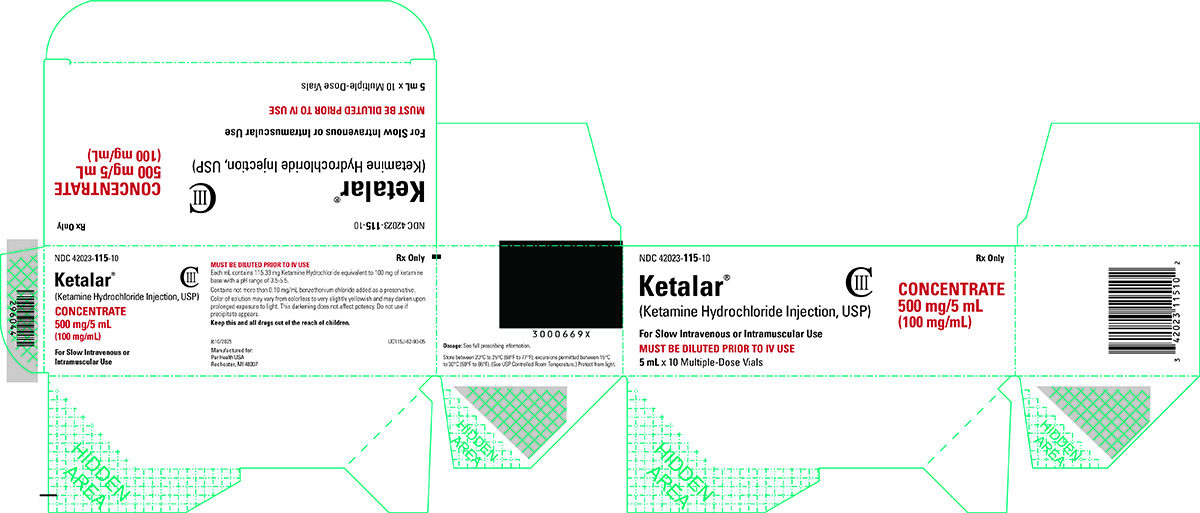 DRUG LABEL: Ketalar
NDC: 42023-113 | Form: INJECTION
Manufacturer: Par Health USA, LLC
Category: prescription | Type: HUMAN PRESCRIPTION DRUG LABEL
Date: 20251017
DEA Schedule: CIII

ACTIVE INGREDIENTS: KETAMINE HYDROCHLORIDE 10 mg/1 mL
INACTIVE INGREDIENTS: BENZETHONIUM CHLORIDE; SODIUM CHLORIDE

HIGHLIGHTS OF PRESCRIBING INFORMATION

These highlights do not include all the information needed to use KETALAR® safely and effectively. See full prescribing information for KETALAR.
KETALAR (ketamine hydrochloride) injection, for intravenous or intramuscular use, CIII
Initial U.S. Approval: 1970

RECENT MAJOR CHANGES

Drug-Induced Liver Injury (5.6) 06/2025

1 INDICATIONS AND USAGE

KETALAR is a general anesthetic indicated:

- as the sole anesthetic agent for diagnostic and surgical procedures that do not require skeletal muscle relaxation (1)
- for the induction of anesthesia prior to the administration of other general anesthetic agents (1)
- as a supplement to other anesthetic agents (1).

2 DOSAGE AND ADMINISTRATION

- See Full Prescribing Information for important dosage and administration instructions. (2)
- Induction of anesthesia:
  --Intravenous route: Initially, 1 to 4.5 mg/kg administered slowly (over a period of 60 seconds). Alternatively, administer a dose of 1 to 2 mg/kg at a rate of 0.5 mg/kg/min. (2.2)
  --Intramuscular route: Initially, 6.5 to 13 mg/kg. (2.2)
- Maintenance of anesthesia: Increments of one-half to the full induction dose may be repeated as needed (2.2). Adjust the dose according to the patient's anesthetic needs and whether an additional anesthetic agent is employed. (2.2)
- Supplement to other anesthetic agents: The regimen of a reduced dose of KETALAR supplemented with diazepam can be used to produce balanced anesthesia by combination with other agents. (2.2)

3 DOSAGE FORMS AND STRENGTHS

Injection: 200 mg/20 mL (10 mg/mL), 500 mg/10 mL (50 mg/mL), and 500 mg/5 mL (100 mg/mL) multiple-dose vials (3).

4 CONTRAINDICATIONS

- In patients for whom a significant elevation of blood pressure would be a serious hazard (4).
- Known hypersensitivity to ketamine or to any excipient (4).

5 WARNINGS AND PRECAUTIONS

- Hemodynamic Instability: Monitor vital signs and cardiac function during KETALAR administration. (5.1)
- Emergence Reactions: Postoperative confusional states may occur during the recovery period. Reduce by minimizing verbal, tactile, and visual stimulation of the patient. (5.2)
- Risk of Respiratory Depression: May occur with overdosage or too rapid a rate of administration. Maintain adequate oxygenation and ventilation. (5.3)
- Risks of KETALAR alone for Procedures of the Pharynx, Larynx, or Bronchial Tree: Pharyngeal and laryngeal reflexes are not suppressed with KETALAR when it is used alone. Avoid use as a sole anesthetic agent in surgery or diagnostic procedures of the pharynx, larynx, or bronchial tree. Muscle relaxants may be required. (5.4)
- Pediatric Neurotoxicity: Long-term cognitive deficits may occur when used for longer than 3 hours in children ≤3 years (5.5)

6 ADVERSE REACTIONS

The most common adverse reactions are emergence reactions and elevated blood pressure and pulse (6).

To report SUSPECTED ADVERSE REACTIONS, contact Par Health at 1-800-828-9393 or FDA at 1-800-FDA-1088 or www.fda.gov/medwatch.

7 DRUG INTERACTIONS

Theophylline or Aminophylline: Do not co-administer with KETALAR as concomitant use may lower the seizure threshold (7.1).

Sympathomimetics and Vasopressin: Closely monitor vital signs when co-administered with KETALAR. Consider dose adjustment individualized to the patient’s clinical situation (7.2).

Benzodiazepines, Opioid Analgesics, or other CNS Depressants: Concomitant use may result in profound sedation, respiratory depression, coma, or death. Concomitant use of opioid analgesics may prolong recovery time. (7.3).

FULL PRESCRIBING INFORMATION

RECENT MAJOR CHANGES

Drug-Induced Liver Injury (5.6) 06/2025

1 INDICATIONS AND USAGE

KETALAR (ketamine hydrochloride) injection is indicated:

- as the sole anesthetic agent for diagnostic and surgical procedures that do not require skeletal muscle relaxation.
- for the induction of anesthesia prior to the administration of other general anesthetic agents.
- as a supplement to other anesthetic agents.

2 DOSAGE AND ADMINISTRATION

2.1 Important Dosage and Administration Information

KETALAR should be administered by or under the direction of physicians experienced in the administration of general anesthetics, maintenance of a patent airway, and oxygenation and ventilation. Continuously monitor vital signs in patients receiving KETALAR.

Emergency airway equipment must be immediately available.

Do not administer the 100 mg/mL concentration of KETALAR intravenously without proper dilution [see Dosage and Administration (2.3)]. Must be used immediately after dilution.

While some degree of airway protection may be afforded due to active laryngeal-pharyngeal reflexes, vomiting and aspiration may occur with KETALAR. KETALAR is not recommended for use in patients who have not followed nil per os guidelines.

Due to the potential for salivation during KETALAR administration, administer an antisialagogue prior to induction of anesthesia.

In individuals with a history of chronic ketamine use for off-label indications, there have been case reports of genitourinary pain that may be related to the ketamine treatment, not the underlying condition [see Adverse Reactions (6)]. Consider cessation of ketamine if genitourinary pain continues in the setting of other genitourinary symptoms.

2.2 Recommended Dosage and Administration

The KETALAR dosage must be individualized and titrated to the desired clinical effect.

If a longer duration of effect is desired, additional increments can be administered intravenously or intramuscularly to maintain anesthesia. However, a higher total dose will result in a longer time to complete recovery.

Induction of Anesthesia

Intravenous Route: The initial dose of KETALAR administered intravenously may range from 1 mg/kg to 4.5 mg/kg. The average amount required to produce 5 to 10 minutes of surgical anesthesia within 30 seconds following injection is 2 mg/kg. Administer KETALAR slowly (i.e., over a period of 60 seconds). Rapid administration may result in respiratory depression and enhanced vasopressor response. The induction dose may be administered as an intravenous infusion at a rate of 0.5 mg/kg/min.

Intramuscular Route: The initial dose of KETALAR administered intramuscularly may range from 6.5 to 13 mg/kg. A dose of 9 to 13 mg/kg usually produces surgical anesthesia within 3 to 4 minutes following injection, with the anesthetic effect usually lasting 12 to 25 minutes. Administer a benzodiazepine, if clinically indicated, for the prevention of neuropsychological manifestations during emergence from anesthesia.

Maintenance of Anesthesia

Adjust the maintenance dose according to the patient's anesthetic needs and whether an additional anesthetic agent is administered.

Repeat increments of one-half to the full induction dose as needed for maintenance of anesthesia. Purposeless and tonic-clonic movements of extremities may occur during the course of ketamine anesthesia. These movements do not imply a light plane and are not indicative of the need for additional doses of the anesthetic.

KETALAR given by slow microdrip infusion technique at a dose of 0.1 to 0.5 mg/minute will maintain general anesthesia in adult patients induced with KETALAR. Augment KETALAR with an intravenous benzodiazepine for the prevention of neuropsychological manifestations during emergence.

Supplement to Other Anesthetic Agents

KETALAR can be administered to supplement other general and local anesthetic agents. Continuously monitor patients for changes in respiratory and hemodynamic parameters.

A reduced dose of KETALAR can be used to produce balanced anesthesia when used in combination with other anesthetic agents.

2.3 Preparation of Dilution

KETALAR is a clear, colorless sterile solution. Parenteral drug products should be inspected visually for particulate matter and discoloration prior to administration, whenever solution and container permit. Discard if product is discolored or contains particulate matter.

Induction of Anesthesia: Do not intravenously inject the 100 mg/mL concentration of KETALAR without proper dilution. Dilute KETALAR with an equal volume of either Sterile Water for injection, USP, 0.9% Sodium Chloride Injection, USP (Normal Saline), or 5% Dextrose in Water. Use immediately after dilution.

Maintenance of Anesthesia: To prepare a dilute solution containing 1 mg of ketamine per mL, aseptically transfer 10 mL from a 50 mg per mL vial or 5 mL from a 100 mg per mL vial to 500 mL of 5% Dextrose Injection, USP or 0.9% Sodium Chloride Injection, USP (Normal Saline) and mix well. The resultant solution will contain 1 mg of ketamine per mL. Use immediately after dilution.

When fluid restriction is required, KETALAR can be added to a 250 mL infusion as described above to provide a KETALAR concentration of 2 mg/mL.

KETALAR 10 mg/mL vials are not recommended for dilution.

3 DOSAGE FORMS AND STRENGTHS

KETALAR injection is a clear, colorless, sterile solution available in multiple-dose vials containing either 10 mg ketamine base (equivalent to 11.53 mg ketamine hydrochloride), 50 mg ketamine base (equivalent to 57.67 mg ketamine hydrochloride) or 100 mg ketamine base (equivalent to 115.33 mg ketamine hydrochloride).

- 200 mg/20 mL (10 mg/mL)
- 500 mg/10 mL (50 mg/mL)
- 500 mg/5 mL (100 mg/mL)

4 CONTRAINDICATIONS

- KETALAR is contraindicated in patients for whom a significant elevation of blood pressure would constitute a serious hazard [see Warnings and Precautions (5.1)].
- KETALAR is contraindicated in patients with known hypersensitivity to ketamine or to any excipient [see Adverse Reactions (6)].

5 WARNINGS AND PRECAUTIONS

5.1 Hemodynamic Instability

Transient increases in blood pressure, heart rate, and cardiac index are frequently observed following administration of KETALAR. Decreases in blood pressure and heart rate, arrhythmias, and cardiac decompensation have also been observed. Monitor vital signs and cardiac function during KETALAR administration. KETALAR is contraindicated in patients for whom a significant elevation of blood pressure would constitute a serious hazard [see Contraindications (4)].

5.2 Emergence Reactions

Emergence delirium (postoperative confusional states or agitation) has occurred in approximately 12% of patients during the recovery period, and the duration is generally a few hours. The neuropsychological manifestations vary in severity between pleasant dream-like states, vivid imagery, hallucinations, and emergence delirium. In some cases, these states have been accompanied by confusion, excitement, and irrational behavior, which have been recalled as unpleasant experiences. No residual psychological effects are known to have resulted from use of KETALAR during induction and maintenance of anesthesia.

Intramuscular administration results in a lower incidence of emergence reactions.

The incidence of psychological manifestations during emergence, particularly dream-like observations and emergence delirium, may be reduced by using lower recommended dosages of KETALAR in conjunction with an intravenous benzodiazepine during induction and maintenance of anesthesia [see Dosage and Administration (2.3)]. Also, these reactions may be reduced if verbal, tactile, and visual stimulation of the patient is minimized during the recovery period. This does not preclude the monitoring of vital signs.

5.3 Respiratory Depression

Respiratory depression may occur with overdosage or a rapid rate of administration of KETALAR. Maintain adequate oxygenation and ventilation.

5.4 Risks of Ketalar Alone for Procedures of the Pharynx, Larynx, or Bronchial Tree

KETALAR does not suppress pharyngeal and laryngeal reflexes. Avoid KETALAR administration as a sole anesthetic agent during procedures of the pharynx, larynx, or bronchial tree, including mechanical stimulation of the pharynx. Muscle relaxants may be required for successful completion of procedures of the pharynx, larynx, or bronchial tree.

5.5 Pediatric Neurotoxicity

Published animal studies demonstrate that the administration of anesthetic and sedation drugs that block NMDA receptors and/or potentiate GABA activity increase neuronal apoptosis in the developing brain and result in long-term cognitive deficits when used for longer than 3 hours. The clinical significance of these findings is not clear. However, based on the available data, the window of vulnerability to these changes is believed to correlate with exposures in the third trimester of gestation through the first several months of life, but may extend out to approximately three years of age in humans [see Use in Specific Populations (8.1, 8.4), Nonclinical Toxicology (13.2)].

Some published studies in children suggest that similar deficits may occur after repeated or prolonged exposures to anesthetic agents early in life and may result in adverse cognitive or behavioral effects. These studies have substantial limitations, and it is not clear if the observed effects are due to the anesthetic/sedation drug administration or other factors such as the surgery or underlying illness.

Anesthetic and sedation drugs are a necessary part of the care of children needing surgery, other procedures, or tests that cannot be delayed, and no specific medications have been shown to be safer than any other. Decisions regarding the timing of any elective procedures requiring anesthesia should take into consideration the benefits of the procedure weighed against the potential risks.

5.6 Drug-Induced Liver Injury

Ketamine administration is associated with hepatobiliary dysfunction (most often a cholestatic pattern), with recurrent use (e.g., misuse/abuse or medically supervised unapproved indications). Biliary duct dilatation and/or biliary duct stricture and/or stenosis with or without evidence of biliary obstruction has also been reported with recurrent use. Obtain baseline LFTs, including alkaline phosphatase and gamma glutamyl transferase, in patients receiving ketamine as part of a treatment plan that utilizes recurrent dosing. Monitor those receiving recurrent ketamine at periodic intervals during treatment.

Reports of ketamine and the occurrence of sclerosing cholangitis have been received. Therefore, consider sclerosing cholangitis in patients with long term ketamine use and a cholestatic pattern of increased LFTs particularly grossly elevated gamma glutamyl transferase and alkaline phosphatase levels.

5.7 Increase in Cerebrospinal Fluid Pressure

An increase in intracranial pressure has been reported following administration of ketamine hydrochloride. Patients with elevated intracranial pressure should be in a monitored setting with frequent neurologic assessments.

5.8 Drug Interactions

Theophylline or Aminophylline: Concomitant administration of KETALAR and theophylline or aminophylline may lower the seizure threshold [see Drug Interactions (7.1)]. Consider using an alternative to KETALAR in patients receiving theophylline or aminophylline.

Sympathomimetics and Vasopressin: Sympathomimetics and vasopressin may enhance the sympathomimetic effects of ketamine [see Drug Interactions (7.2)]. Closely monitor vital signs when KETALAR and sympathomimetics or vasopressin are co-administered and consider dose adjustment individualized to the patient’s clinical situation.

Benzodiazepines, Opioid Analgesics, or Other CNS Depressants

Concomitant use of ketamine with opioid analgesics, benzodiazepines, or other central nervous system (CNS) depressants, including alcohol, may result in profound sedation, respiratory depression, coma, and death [see Drug Interactions (7.3)]. Closely monitor neurological status and respiratory parameters, including respiratory rate and pulse oximetry, when KETALR and opioid analgesics, benzodiazepines, or other CNS depressants are co-administered. Consider dose adjustment individualized to the patient’s clinical situation.

6 ADVERSE REACTIONS

The following clinically significant adverse reactions are described elsewhere in the labeling:

- Hemodynamic Instability [see Warnings and Precautions (5.1)]
- Emergence Reactions [see Warnings and Precautions (5.2)]
- Respiratory Depression [see Warnings and Precautions (5.3)]
- Pediatric Neurotoxicity [see Warnings and Precautions (5.5)]
- Drug-Induced Liver Injury [see Warnings and Precautions (5.6)]

The following adverse reactions associated with the use of KETALAR were identified in clinical studies or postmarketing reports. Because some of these reactions were reported voluntarily from a population of uncertain size, it is not always possible to reliably estimate their frequency or establish a causal relationship to drug exposure.

Cardiovascular disorders: Elevated blood pressure, heart rate, and cardiac index; decreases in blood pressure and heart rate; arrhythmias; cardiac decompensation (in patients with suspected catecholamine depletion).

Eye disorders: Diplopia, nystagmus, elevation in intraocular pressure.

Gastrointestinal disorders: Anorexia, nausea, vomiting, hepatobiliary dysfunction. Biliary duct dilatation and/or biliary duct stricture and/or stenosis with or without evidence of biliary obstruction and secondary sclerosing cholangitis has been reported with recurrent use (e.g., misuse/abuse or medically supervised unapproved indications).

Administration site disorders: Local pain and exanthema at the injection site.

Immune system disorders: Anaphylaxis.

Neurologic disorders: Emergence reactions (post-operative delirium), [see Warnings and Precautions (5.2)]. During administration, enhanced muscle tone and spasms (resembling a partial motor or generalized motor seizure).

Psychiatric disorders: Adverse psychiatric events have occurred and/or persisted days to weeks after ketamine exposure.

Renal and urinary disorders: In individuals with history of chronic ketamine use or abuse, lower urinary tract and bladder symptoms including dysuria, increased urinary frequency, urgency, urge incontinence, and hematuria have been reported [see Dosage and Administration (2.1)]. In addition, diagnostic studies performed to assess the cause of these symptoms have reported cystitis (including cystitis non-infective, cystitis interstitial, cystitis ulcerative, cystitis erosive and cystitis hemorrhagic), ureteric stenosis (strictures), ureteric obstruction as well as hydronephrosis and reduced bladder capacity.

Respiratory disorders: Respiratory depression and apnea following rapid intravenous administration of high doses of KETALAR; laryngospasm, and airway obstruction.

Skin and subcutaneous tissue disorders: Transient erythema and/or morbilliform rash

7 DRUG INTERACTIONS

7.1 Theophylline or Aminophylline

Concomitant administration of KETALAR and theophylline or aminophylline may lower the seizure threshold. Consider using an alternative to KETALAR in patients receiving theophylline or aminophylline.

7.2 Sympathomimetics and Vasopressin

Sympathomimetics and vasopressin may enhance the sympathomimetic effects of ketamine. Closely monitor vital signs when KETALAR and sympathomimetics or vasopressin are co-administered and consider dose adjustment individualized to the patient’s clinical situation.

7.3 Benzodiazepines, Opioid Analgesics, Or Other CNS Depressants

Concomitant use of ketamine with opioid analgesics, benzodiazepines, or other central nervous system (CNS) depressants, including alcohol, may result in profound sedation, respiratory depression, coma, and death [see Warnings and Precautions (5.8)].

Opioid analgesics administered concomitantly with KETALAR may prolong time to complete recovery from anesthesia.

8 USE IN SPECIFIC POPULATIONS

8.1 Pregnancy

Risk Summary

Available data on the use of ketamine in pregnant women mostly describe its use at the time of cesarean section and have not identified a drug-associated risk of adverse maternal or fetal outcomes. The data are limited by retrospective collection, small sample sizes, and a lack of long-term follow-up. There are no available data on ketamine use during other stages of pregnancy to allow for an evaluation of drug-associated risk of major birth defects or miscarriage.

In animal reproduction studies in rats developmental delays (hypoplasia of skeletal tissues) were noted at 0.3 times the human intramuscular dose of 10 mg/kg. In rabbits, developmental delays and increased fetal resorptions were noted at 0.6 times the human dose. Published studies in pregnant primates demonstrate that the administration of anesthetic and sedation drugs that block NMDA receptors and/or potentiate GABA activity during the period of peak brain development increases neuronal apoptosis in the developing brain of the offspring when used for longer than 3 hours. There are no data on pregnancy exposures in primates corresponding to periods prior to the third trimester in humans. The clinical significance of these nonclinical findings is not known, and the benefits of appropriate anesthesia in pregnant women who require procedures should be balanced with the potential risks suggested by the nonclinical data.

The estimated background risk of major birth defects and miscarriage for the indicated population is unknown. All pregnancies have a background risk of birth defect, loss, or other adverse outcomes. In the U.S. general population, the estimated background risk of major birth defects and miscarriage in clinically recognized pregnancies is 2-4% and 15-20%, respectively.

Data

Animal Data

Pregnant rats were treated intramuscularly with 20 mg/kg ketamine (0.3 times the human dose of 10 mg/kg IM based on body surface area) on either Gestation Days 6 to 10 or Gestation Days 11 to 15. Ketamine treatment produced an increased incidence of hypoplastic skull, phalanges, and sternebrae in the pups.

Pregnant rabbits were treated intramuscularly with 20 mg/kg ketamine (0.6 times the human dose of 10 mg/kg IM based on body surface area) on either Gestation Days 6 to 10 or Gestation Days 11 to 15. An increase in resorptions and skeletal hypoplasia of the fetuses were noted. Additional pregnant rabbits were treated intramuscularly with a single dose 60 mg/kg (1.9 times the human dose of 10 mg/kg IM based on body surface area) on Gestation Day 6 only. Skeletal hypoplasia was reported in the fetuses.

In a study where pregnant rats were treated intramuscularly with 20 mg/kg ketamine (0.3 times the human dose of 10 mg/kg IM based on body surface area) from Gestation Day 18 to 21. There was a slight increase in incidence of delayed parturition by one day in treated dams of this group. No adverse effects on the litters or pups were noted; however, learning and memory assessments were not completed.

Three (3) pregnant beagle dogs were treated intramuscularly with 25 mg/kg ketamine (1.3 times the human dose of 10 mg/kg IM based on body surface area) twice weekly for the three weeks of the first, second, and third trimesters of pregnancy, respectively, without the development of adverse effects in the pups.

In a published study in primates, administration of an anesthetic dose of ketamine for 24 hours on Gestation Day 122 increased neuronal apoptosis in the developing brain of the fetus. In other published studies, administration of either isoflurane or propofol for 5 hours on Gestation Day 120 resulted in increased neuronal and oligodendrocyte apoptosis in the developing brain of the offspring. With respect to brain development, this time period corresponds to the third trimester of gestation in the human. The clinical significance of these findings is not clear; however, studies in juvenile animals suggest neuroapoptosis correlates with long-term cognitive deficits [see Warnings and Precautions (5.5), Use in Specific Populations (8.4), and Nonclinical Toxicology (13.2)].

8.2 Lactation

Risk Summary

Published literature describe the presence of ketamine and its metabolite in human milk. There are no data on the effects on the breastfed infants; however, infants should be monitored for sedation, respiratory depression, and increased muscle tone and spasms. There are no data on the effects of ketamine on milk production. Due to the potential for developmental neurotoxicity of ketamine in newborns and infants [see subsection (8.4)], KETALAR treatment in lactating women should be limited to anesthesia. The developmental and health benefits of breastfeeding should be considered along with the mother’s clinical need for ketamine and any potential adverse effects on the breastfed child from ketamine or from the underlying maternal condition.

8.4 Pediatric Use

Safety and effectiveness in pediatric patients below the age of 16 have not been established.

Published juvenile animal studies demonstrate that the administration of anesthetic and sedation drugs, such as KETALAR, that either block NMDA receptors or potentiate the activity of GABA during the period of rapid brain growth or synaptogenesis, results in widespread neuronal and oligodendrocyte cell loss in the developing brain and alterations in synaptic morphology and neurogenesis. Based on comparisons across species, the window of vulnerability to these changes is believed to correlate with exposures in the third trimester of gestation through the first several months of life but may extend out to approximately 3 years of age in humans.

In primates, exposure to 3 hours of ketamine that produced a light surgical plane of anesthesia did not increase neuronal cell loss, however, treatment regimens of 5 hours or longer of isoflurane increased neuronal cell loss. Data from isoflurane-treated rodents and ketamine-treated primates suggest that the neuronal and oligodendrocyte cell losses are associated with prolonged cognitive deficits in learning and memory. The clinical significance of these nonclinical findings is not known, and healthcare providers should balance the benefits of appropriate anesthesia in neonates and young children who require procedures with the potential risks suggested by the nonclinical data [see Warnings and Precautions (5.5), Use in Specific Populations (8.1), and Nonclinical Toxicology (13.2)].

8.5 Geriatric Use

Clinical studies of ketamine hydrochloride did not include sufficient numbers of subjects aged 65 and over to determine whether they respond differently from younger subjects. Other reported clinical experience has not identified differences in responses between the elderly and younger patients. In general, dose selection for an elderly patient should be cautious, usually starting at the low end of the dosing range, reflecting the greater frequency of decreased hepatic, renal, or cardiac function, and of concomitant disease or other drug therapy.

9 DRUG ABUSE AND DEPENDENCE

9.1 Controlled Substance

KETALAR contains ketamine, a Schedule III controlled substance under the Controlled Substance Act.

9.2 Abuse

Individuals with a history of drug abuse or dependence may be at greater risk for abuse and misuse of KETALAR. Abuse is the intentional, non-therapeutic use of a drug, even once, for its psychological or physiological effects. Misuse is the intentional use, for therapeutic purposes, of a drug by an individual in a way other than prescribed by a health care provider or for whom it was not prescribed.

In a context of drug abuse, KETALAR may produce a variety of symptoms including anxiety, dysphoria, disorientation, insomnia, flashback, hallucinations, and feelings of floating, detachment and being “spaced out”.

Recurrent high-dose ketamine misuse or abuse may be associated with memory and/or attention impairment.

9.3 Dependence

Physical dependence has been reported with prolonged use of ketamine. Physical dependence is a state that develops as a result of physiological adaptation in response to repeated drug use, manifested by withdrawal signs and symptoms after abrupt discontinuation or significant dosage reduction of a drug. Withdrawal symptoms have been reported after the discontinuation of frequently used (more than weekly), large doses of ketamine for long periods of time. Reported symptoms of withdrawal associated with daily intake of large doses of ketamine include craving, fatigue, poor appetite, and anxiety.

Tolerance has been reported with prolonged use of ketamine. Tolerance is a physiological state characterized by a reduced response to a drug after repeated administration (i.e., a higher dose of a drug is required to produce the same effect that was once obtained at a lower dose).

10 OVERDOSAGE

Changes in heart rate and blood pressure, respiratory depression, and apnea may occur with overdosage or by a rapid rate of administration of KETALAR. Monitor patients for clinically relevant changes in heart rate and blood pressure. Assisted ventilation, including mechanical ventilation, may be required.

In cases of unintentional overdose of KETALAR (up to ten times that usually required), patients had a prolonged but complete recovery.

11 DESCRIPTION

KETALAR (ketamine hydrochloride) injection, for intravenous or intramuscular use, contains ketamine, a nonbarbiturate general anesthetic. Ketamine hydrochloride, USP is a white crystalline powder and has a molecular formula of C13H16ClNO•HCl and a molecular weight of 274.19. The chemical name for ketamine hydrochloride is (±)-2-(o-Chlorophenyl)-2-(methylamino)cyclohexanone hydrochloride. The chemical structure of ketamine hydrochloride is:

It is formulated as a slightly acidic (pH 3.5-5.5) sterile solution for intravenous or intramuscular injection. Each milliliter (mL) of the multiple-dose vials contain either 10 mg ketamine base (equivalent to 11.53 mg ketamine hydrochloride), 50 mg ketamine base (equivalent to 57.67 mg ketamine hydrochloride) or 100 mg ketamine base (equivalent to 115.33 mg ketamine hydrochloride) and not more than 0.10 mg/mL benzethonium chloride added as a preservative in water for injection. The 10 mg/mL solution has been made isotonic with 6.60 mg sodium chloride.

12 CLINICAL PHARMACOLOGY

12.1 Mechanism of Action

KETALAR, a racemic mixture of ketamine, is a non-selective, non-competitive antagonist of the N-methyl-D-aspartate (NMDA) receptor, an ionotropic glutamate receptor. The major circulating metabolite of ketamine (norketamine) demonstrated activity at the same receptor with less affinity. Norketamine is about 1/3 as active as ketamine in reducing halothane requirements (MAC) of the rat.

12.2 Pharmacodynamics

Nervous System

Ketamine is a rapidly-acting general anesthetic producing a dissociative anesthetic state characterized by profound analgesia, normal pharyngeal-laryngeal reflexes, normal or slightly enhanced skeletal muscle tone, cardiovascular and respiratory stimulation, and occasionally a transient and minimal respiratory depression. The mechanism of action is primarily due to antagonism of N-methyl-D-aspartate (NMDA receptors) in the central nervous system.

Ketamine can produce nystagmus with pupillary dilation, salivation, lacrimation, and spontaneous limb movements with increased muscle tone through indirect sympathomimetic activity. Ketamine produces analgesia. Ketamine-induced emergence delirium can be reduced with benzodiazepines.

Cardiovascular System

Ketamine increases blood pressure, heart rate, and cardiac output. Cardiovascular effects of ketamine are indirect and believed to be mediated by inhibition of both central and peripheral catecholamine reuptake. Elevation of blood pressure reaches a maximum within a few minutes of injection and usually returns to preanesthetic values within 15 minutes. In the majority of cases, the systolic and diastolic blood pressure peaks from 10% to 50% above preanesthetic levels shortly after induction of anesthesia, but the elevation can be higher or longer in individual cases.

Respiratory System

Ketamine is a potent bronchodilator suitable for anesthetizing patients at high risk for bronchospasm.

12.3 Pharmacokinetics

Distribution

Following intravenous administration, the ketamine concentration has an initial slope (alpha phase) lasting about 45 minutes with a half-life of 10 to 15 minutes. This first phase corresponds clinically to the anesthetic effect of the drug.

Elimination

Metabolism

Ketamine is metabolized via N-dealkylation to the active metabolite norketamine primarily by CYP2B6 and CYP3A4 and to a lesser extent by other CYP enzymes. Norketamine undergoes hydroxylation of the cyclohexone ring to form hydroxynorketamine compounds via CYP-dependent pathways, which are conjugated with glucuronic acid and subsequently undergo dehydration of the hydroxylated metabolites to form the cyclohexene derivative dehydroxynorketamine.

Excretion

Following intravenous administration, the ketamine concentration decreases due to a combination of redistribution from the CNS to slower equilibrating peripheral tissues and hepatic biotransformation to norketamine. The redistribution half-life of ketamine from the CNS to slower equilibrating peripheral tissues (beta phase) is 2.5 hours.

13 NONCLINICAL TOXICOLOGY

13.1 Carcinogenesis, Mutagenesis, Impairment of Fertility

Carcinogenesis

Long-term animal studies have not been conducted to evaluate the carcinogenic potential of ketamine.

Mutagenesis

In a published report, ketamine was clastogenic in the in vitro chromosomal aberration assay.

Impairment of Fertility

Adequate studies to evaluate the impact of ketamine on male or female fertility have not been conducted. Male and female rats were treated with 10 mg/kg ketamine IV (0.8 times the average human induction dose of 2 mg/kg IV based on body surface area) on Days 11, 10, and 9 prior to mating. No impact on fertility was noted; however, this study design does not adequately characterize the impact of a drug on fertility endpoints.

13.2 Animal Toxicology and/or Pharmacology

Published studies in animals demonstrate that the use of anesthetic agents during the period of rapid brain growth or synaptogenesis results in widespread neuronal and oligodendrocyte cell loss in the developing brain and alterations in synaptic morphology and neurogenesis. Based on comparisons across species, the window of vulnerability to these changes is believed to correlate with exposures in the third trimester through the first several months of life, but may extend out to approximately 3 years of age in humans.

In primates, exposure to 3 hours of an anesthetic regimen that produced a light surgical plane of anesthesia did not increase neuronal cell loss, however, treatment regimens of 5 hours or longer increased neuronal cell loss. Data in rodents and in primates suggest that the neuronal and oligodendrocyte cell losses are associated with subtle but prolonged cognitive deficits in learning and memory. The clinical significance of these nonclinical findings is not known, and healthcare providers should balance the benefits of appropriate anesthesia in neonates and young children who require procedures against the potential risks suggested by the nonclinical data [see Warnings and Precautions (5.5), Use in Specific Populations (8.1, 8.4)].

In published studies, intraperitoneal administration of ketamine at doses greater than 40 mg/kg induced vacuolation in neuronal cells of the posterior cingulate and retrosplenial cortices in adult rats, similar to what has been reported in rodents administered other NMDA receptor antagonists. These vacuoles were demonstrated to be reversible and did not progress to degeneration or neuronal death up to doses of 80 mg/kg (1.2 times the human dose of 10 mg/kg based on body surface area). A no-effect level for neuronal vacuolation was 20 mg/kg intraperitoneal (0.3 times a human dose of 10 mg/kg on a body surface area basis). The window of vulnerability to these changes is believed to correlate with exposures in humans from the onset of puberty through adulthood. The relevance of this finding to humans is unknown.

14 CLINICAL STUDIES

KETALAR has been studied in over 12,000 operative and diagnostic procedures, involving over 10,000 patients in 105 separate studies. During the course of these studies, KETALAR was administered as the sole general anesthetic, as an induction agent prior to administration of other general anesthetics, or to supplement other anesthetic agents.

KETALAR has been evaluated during the following procedures:

1. debridement, dressing changes, and skin grafting in burn patients, as well as other superficial surgical procedures.
2. neurodiagnostic procedures such as myelograms and lumbar punctures.
3. diagnostic and operative procedures of the ear, nose, and mouth, including dental extractions.
4. sigmoidoscopy and minor surgery of the anus and rectum, and circumcision.
5. extraperitoneal procedures, such as dilatation and curettage.
6. orthopedic procedures such as closed reductions, manipulations, femoral pinning, amputations, and biopsies.
7. cardiac catheterization procedures.

16 HOW SUPPLIED/STORAGE AND HANDLING

How Supplied

KETALAR injection is a clear, colorless solution supplied as the hydrochloride salt in concentrations equivalent to ketamine base, as follows:

Unit of sale | Strength
NDC 42023-113-10; Unit of 10 | 200 mg in 20 mL multiple- dose vial (10 mg/mL); 10 mg ketamine base (equivalent to 11.53 mg ketamine hydrochloride)
NDC 42023-114-10; Unit of 10 | 500 mg in 10 mL multiple- dose vial (50 mg/mL); 50 mg ketamine base (equivalent to 57.67 mg ketamine hydrochloride)
NDC 42023-115-10; Unit of 10 | 500 mg in 5 mL multiple- dose vial (100 mg/mL); 100 mg ketamine base (equivalent to 115.33 mg ketamine hydrochloride)

Storage and Handling

KETALAR injection should be stored at 20°C to 25°C (68°F to 77°F); excursions permitted between 15°C to 30°C (59°F to 86°F) [see USP Controlled Room Temperature]. Protect from light.

17 PATIENT COUNSELING INFORMATION

- Studies conducted in young animals and children suggest repeated or prolonged use of general anesthetic or sedation drugs in children younger than 3 years may have negative effects on their developing brains. Discuss with parents and caregivers the benefits, risks, and timing and duration of surgery or procedures requiring anesthetic and sedation drugs [see Warnings and Precautions (5.5)].

- Due to the residual anesthetic effects and the potential for drowsiness, advise patients not to drive an automobile, operate hazardous machinery, or engage in hazardous activities within 24 hours of receiving KETALAR.

Manufactured for:

Par Health USA

Rochester, MI 48307

© 2025 Par Health, Inc. or one of its affiliates.

R10/2025